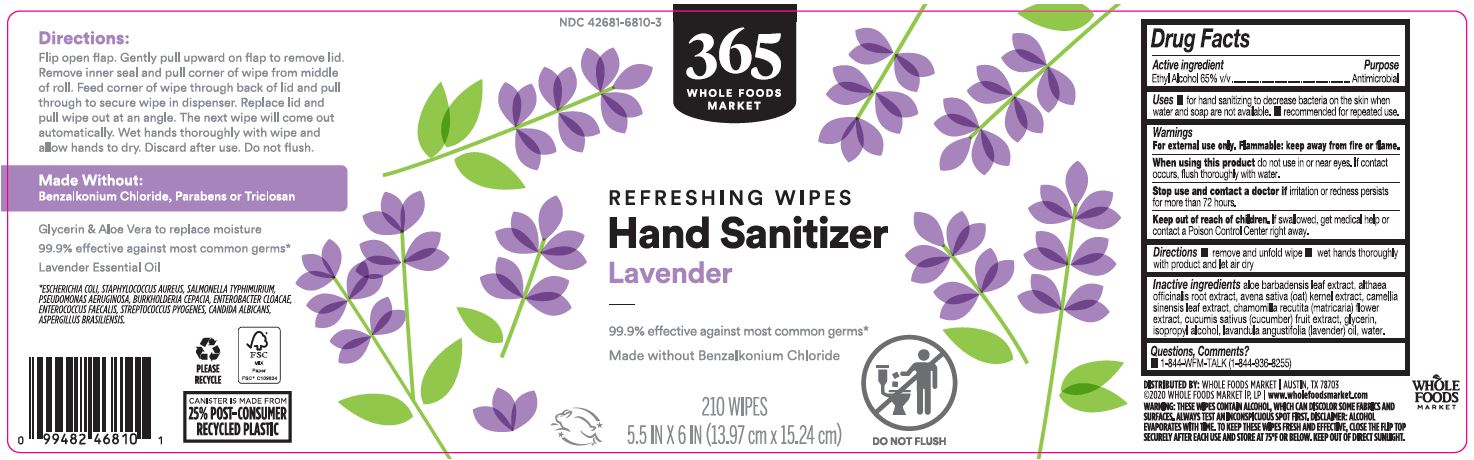 DRUG LABEL: Lavender Hand Sanitizing Wipes
NDC: 42681-6810 | Form: CLOTH
Manufacturer: Whole Foods Market, Inc.
Category: otc | Type: HUMAN OTC DRUG LABEL
Date: 20251120

ACTIVE INGREDIENTS: ALCOHOL 65 mL/100 mL
INACTIVE INGREDIENTS: OAT KERNEL OIL; WATER; ALOE VERA LEAF; ALTHAEA OFFICINALIS ROOT; GLYCERIN; TEA LEAF; MATRICARIA CHAMOMILLA FLOWERING TOP; CUCUMIS SATIVUS WHOLE; ISOPROPYL ALCOHOL; LAVENDER OIL

365 Lavender Hand Sanitizer Wipes 210ct

Active Ingredient

Ethyl Alcohol 65% v/v

Purpose

Antimicrobial

Uses

• for hand sanitizing to decrease bacteria on skin when water and soap are not avaliable

• recommended for repeated use

Warnings

For external use only.

Flammable keep away from fire or flame.

When using this product do not use in or near eyes, if contact occurs, flush thoroughly with water.

Stop use and contact a doctor if irritation or redness persists for more than 72 hours.

Keep out of reach of children. If swallowed, get medical help or contact a Poison Control Center right away

Directions

• remove and unfold wipe

•wet hands thoroughly with product and let air dry

Inactive ingredients

Aloe Barbadensis Leaf Extract
Althaea Officinalis Root Extract
Avena Sativa (Oat) Kernel Extract
Camellia Sinensis Leaf Extract
Chamomilla Recutita (Matricaria) Flower Extract
Cucumis Sativus (Cucumber) Fruit Extract
Glycerin,

Isopropyl alcohol,

Lavandula Angustifolia(Lavender) Oil,

Water.

Questions, Comments?

1-844-WFM-TALK(1-844-936-8255)

Label

NDC 42681-6810-3

365 WHOLE FOODS MARKET

REFRESHING WIPES

Hand Sanitizer

Lavender

99.9% effective against most common germs*

Made without Benzalkonium Chloride

210 WIPES

5.5IN x 6IN (13.97cm x 15.24cm)

DO NOT FLUSH

DISTRIBUTED BY: WHOLE FOODS MARKET | AUSTIN, TX 78703

2020 WHOLE FOODS MARKET IP, LP | www.wholefoodsmarket.com

WARNING: THESE WIPES CONTAIN ALCOHOL, WHICH CAN DISCOLOR SOME FABRICS AND SURFACES. ALWAYS TEST AN INCONSPICUOUS SPOT FIRST. DISCLAIMER: ALCOHOL EVAPORATES WITH TIME. TO KEEP THESE WIPES FRESH AND EFFECTIVE, CLOSE THE FLIP TOP SECURELY AFTER EACH USE AND STORE AT 75F OR BELOW. KEEP OUT OF DIRECT SUNLIGHT.

Directions:

Flip open flap. Gently pull upward on flap to remove lid. Remove inner seal and pull corner of wipe from middle of roll. Feed corner of wipe through back of lid and pull through to secure wipe in dispenser. Replace lid and pull wipe out at an angle. The next wipe will come out automatically. Wet hands thoroughly with wipe and allow hands to dry. Discard after use. Do not flush.

Made Without:

Benzalkonium Chloride, Parabens or Triclosan

Glycerin & Aloe Vera to replace moisture

99.9% effective against most common germs*

Lavender Essential Oil

PLEASE RECYCLE

FSC MIX Paper

FSC C109834

UPC 099482468101

CANISTER IS MADE FROM 25% POST-CONSUMER RECYLED PLASTIC